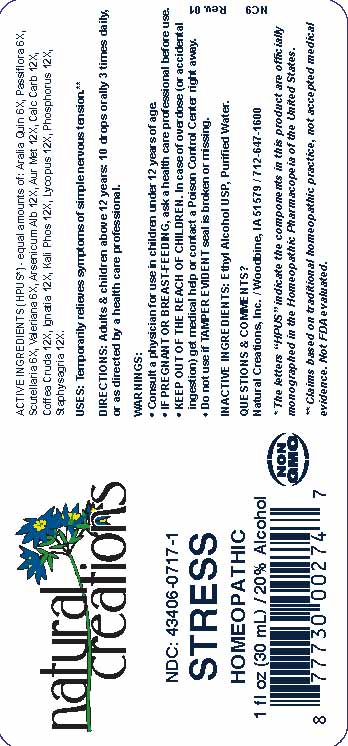 DRUG LABEL: Stress
NDC: 43406-0717 | Form: LIQUID
Manufacturer: Natural Creations, Inc
Category: homeopathic | Type: HUMAN OTC DRUG LABEL
Date: 20251216

ACTIVE INGREDIENTS: AMERICAN GINSENG 6 [hp_X]/1 mL; PASSIFLORA INCARNATA FLOWERING TOP 6 [hp_X]/1 mL; SCUTELLARIA LATERIFLORA WHOLE 6 [hp_X]/1 mL; VALERIAN 6 [hp_X]/1 mL; ARSENIC TRIOXIDE 12 [hp_X]/1 mL; GOLD 12 [hp_X]/1 mL; OYSTER SHELL CALCIUM CARBONATE, CRUDE 12 [hp_X]/1 mL; ARABICA COFFEE BEAN 12 [hp_X]/1 mL; STRYCHNOS IGNATII SEED 12 [hp_X]/1 mL; DIBASIC POTASSIUM PHOSPHATE 12 [hp_X]/1 mL; LYCOPUS VIRGINICUS WHOLE 12 [hp_X]/1 mL; PHOSPHORUS 12 [hp_X]/1 mL; DELPHINIUM STAPHISAGRIA SEED 12 [hp_X]/1 mL
INACTIVE INGREDIENTS: ALCOHOL; WATER

Stress

ACTIVE INGREDIENT

ACTIVE INGREDIENTS (HPUS*) - equal amounts of: Aralia Quin 6X, Passiflora 6X, Scutellaria 6X, Valeriana 6X, Arsenicum Alb 12X, Aur Met 12X, Calc Carb 12X, Coffea Cruda 12X, Ignatia 12X, Kali Phos 12X, Lycopus 12X, Phosphorus 12X, Staphysagria 12X

INDICATIONS AND USAGE

USES: Temporarily relieves symptoms of simple nervous tension.**

PURPOSE

USES: Temporarily relieves symptoms of simple nervous tension.**

DOSAGE AND ADMINISTRATION

DIRECTIONS: Adults & children above 12 years: 10 drops orally 3 times daily, or as directed by a health care professional.

KEEP OUT OF REACH OF CHILDREN

KEEP OUT OF THE REACH OF CHILDREN. In case of overdose (or accidental ingestion) get medical help or contact a Poison Control Center right away.

WARNINGS:

- Consult a physician for use in children under 12 years of age.
- IF PREGNANT OR BREAST-FEEDING, ask a health care professional before use.
- KEEP OUT OF THE REACH OF CHILDREN. In case of overdose (or accidental ingestion) get medical help or contact a Poison Control Center right away.
- Do not use if TAMPER EVIDENT seal is broken or missing.

INACTIVE INGREDIENTS: Ethyl Alcohol USP, Purified Water

QUESTIONS & COMMENTS?

Natural Creations, Inc. / Woodbine, IA 51579 / 712-647-1600

REFERENCES

*The letters "HPUS" indicate the components in the product are officially monographed in the Homeopathic Pharmacopeia of the United States.

**Claims based on traditional homeopathic practice, not accepted medical evidence. Not FDA evaluated.

PACKAGE LABEL

NDC:43406-0717-1

Stress

HOMEOPATHIC

1 fl oz (30mL) / 20% Alcohol